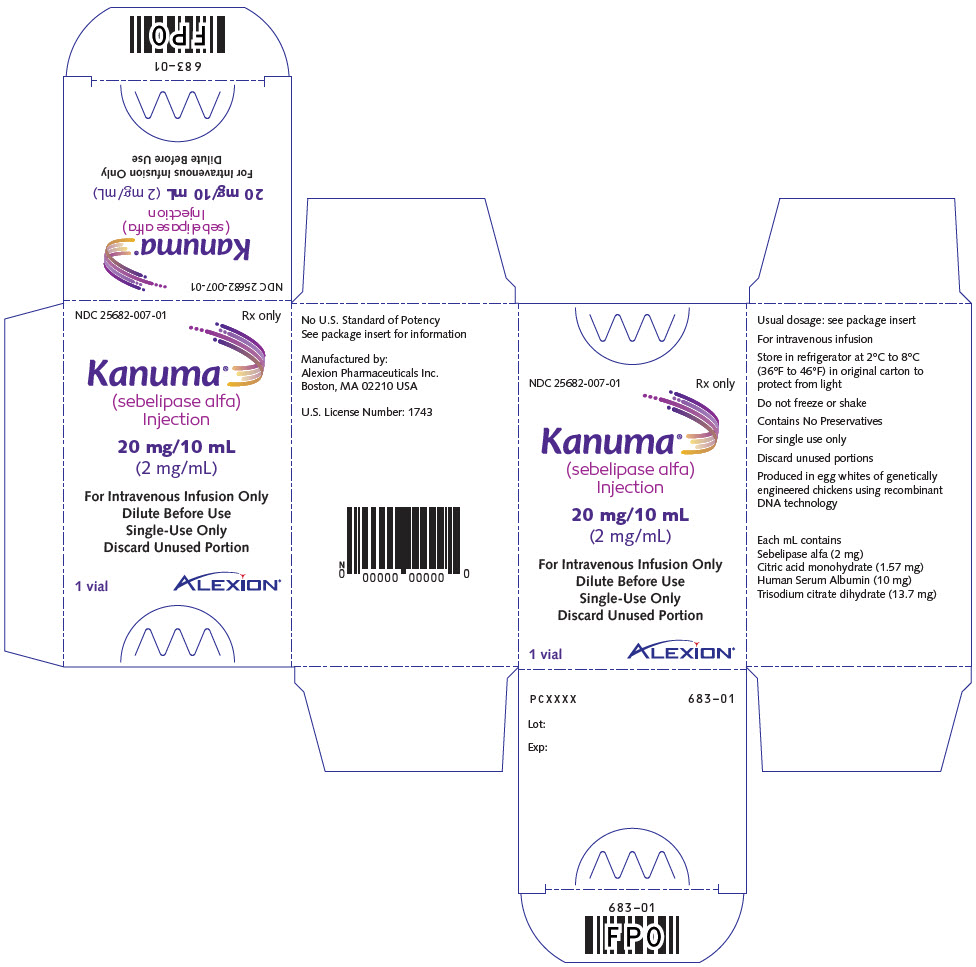 DRUG LABEL: KANUMA
NDC: 25682-007 | Form: INJECTION, SOLUTION, CONCENTRATE
Manufacturer: Alexion Pharmaceuticals, Inc.
Category: prescription | Type: HUMAN PRESCRIPTION DRUG LABEL
Date: 20250721

ACTIVE INGREDIENTS: Sebelipase alfa 2 mg/1 mL
INACTIVE INGREDIENTS: Trisodium citrate dihydrate; Citric acid monohydrate; Albumin Human

HIGHLIGHTS OF PRESCRIBING INFORMATION

These highlights do not include all the information needed to use KANUMA safely and effectively. See full prescribing information for KANUMA.
KANUMA (sebelipase alfa) injection, for intravenous use
Initial U.S. Approval: 2015

WARNING: HYPERSENSITIVITY REACTIONS INCLUDING ANAPHYLAXIS

See full prescribing information for complete boxed warning.

- Anaphylaxis has occurred during the early course of enzyme replacement therapy and after extended duration of therapy. (5.1)
- Initiate KANUMA in a healthcare setting with appropriate medical monitoring and support measures, including access to cardiopulmonary resuscitation. (5.1)
- If a severe hypersensitivity reaction (e.g., anaphylaxis) occurs, discontinue KANUMA and immediately initiate appropriate medical treatment, including use of epinephrine. (5.1)

RECENT MAJOR CHANGES

Boxed Warning | 7/2024
Dosage and Administration (2.1) | 7/2024
Warnings and Precautions (5.1) | 7/2024

1 INDICATIONS AND USAGE

KANUMA® is a hydrolytic lysosomal cholesteryl ester and triacylglycerol-specific enzyme indicated for the treatment of patients with a diagnosis of Lysosomal Acid Lipase (LAL) deficiency. (1)

2 DOSAGE AND ADMINISTRATION

Administration of KANUMA should be supervised by a healthcare provider knowledgeable in the management of hypersensitivity reactions including anaphylaxis. (2.1)

Infants with Rapidly Progressive LAL Deficiency Presenting within the First 6 Months of Life:

- The recommended starting dosage is 1 mg/kg as an intravenous infusion once weekly. (2.2)
- For patients with a suboptimal clinical response, increase the dosage to 3 mg/kg once weekly. (2.2)
- For patients with continued suboptimal clinical response, further increase the dosage to 5 mg/kg once weekly. (2.2)

Pediatric and Adult Patients with LAL Deficiency:

- The recommended dosage is 1 mg/kg as an intravenous infusion once every other week. (2.2)
- For patients with a suboptimal clinical response, increase the dosage to 3 mg/kg once every other week. (2.2)

See Full Prescribing Information for complete Dosage and Administration Information.

Administration Instructions

- Infuse over at least 2 hours. (2.4)
- Consider further prolonging the infusion time for patients receiving dosages greater than 1 mg/kg or for those who have experienced a hypersensitivity reaction. (2.4)
- Consider a 1-hour infusion for the 1 mg/kg dose in patients who tolerate the infusion. (2.4)

3 DOSAGE FORMS AND STRENGTHS

Injection: 20 mg/10 mL (2 mg/mL) solution in single-dose vials. (3)

4 CONTRAINDICATIONS

None. (4)

5 WARNINGS AND PRECAUTIONS

- Hypersensitivity to Eggs or Egg Products: Consider the risks and benefits of treatment in patients with known systemic hypersensitivity reactions to eggs or egg products. (5.2)

6 ADVERSE REACTIONS

The most common adverse reactions are:

- Infants with Rapidly Progressive LAL Deficiency Presenting within the First 6 Months of Life (≥30%): diarrhea, vomiting, fever, rhinitis, anemia, cough, nasopharyngitis, and urticaria. (6.1)
- Pediatric and Adult Patients with LAL Deficiency (≥8%): headache, fever, oropharyngeal pain, nasopharyngitis, asthenia, constipation, and nausea. (6.1)

To report SUSPECTED ADVERSE REACTIONS, contact Alexion at 1-844-259-6783 or FDA at 1-800-FDA-1088 or www.fda.gov/medwatch

FULL PRESCRIBING INFORMATION

WARNING: HYPERSENSITIVITY REACTIONS INCLUDING ANAPHYLAXIS

Patients treated with enzyme replacement therapies have experienced life-threatening hypersensitivity reactions, including anaphylaxis. Anaphylaxis has occurred during the early course of enzyme replacement therapy and after extended duration of therapy.

Initiate KANUMA in a healthcare setting with appropriate medical monitoring and support measures, including access to cardiopulmonary resuscitation equipment. If a severe hypersensitivity reaction (e.g., anaphylaxis) occurs, discontinue KANUMA and immediately initiate appropriate medical treatment, including use of epinephrine. Inform patients of the symptoms of life-threatening hypersensitivity reactions, including anaphylaxis and to seek immediate medical care should symptoms occur [see Warnings and Precautions (5.1)].

1 INDICATIONS AND USAGE

KANUMA® is indicated for the treatment of patients with a diagnosis of Lysosomal Acid Lipase (LAL) deficiency.

2 DOSAGE AND ADMINISTRATION

2.1 Recommendations Prior to KANUMA Treatment

Administration of KANUMA should be supervised by a healthcare provider knowledgeable in the management of hypersensitivity reactions including anaphylaxis [see Warnings and Precautions (5.1)].

Initiate KANUMA in a healthcare setting with appropriate medical monitoring and support measures, including access to cardiopulmonary resuscitation equipment [see Warnings and Precautions (5.1)].

2.2 Recommended Dosage

Infants with Rapidly Progressive LAL Deficiency Presenting within the First 6 Months of Life:

- The recommended starting dosage is 1 mg/kg administered as an intravenous infusion once weekly.
- For patients with a suboptimal clinical response, increase the dosage to 3 mg/kg once weekly.
- For patients with continued suboptimal clinical response on the 3 mg/kg once weekly dosage, further increase the dosage to 5 mg/kg once weekly.
- A suboptimal clinical response is defined as any of the following: poor growth, deteriorating biochemical markers, or persistent or worsening organomegaly.

Pediatric and Adult Patients with LAL Deficiency:

- The recommended dosage is 1 mg/kg administered as an intravenous infusion once every other week.
- For patients with a suboptimal clinical response, increase the dosage to 3 mg/kg once every other week.
- A suboptimal clinical response is defined as any of the following: poor growth, deteriorating biochemical markers [e.g., alanine aminotransferase (ALT), aspartate aminotransferase (AST)], and/or parameters of lipid metabolism [e.g., low-density lipoprotein cholesterol (LDL-c), triglycerides (TG)].

2.3 Preparation Instructions

KANUMA is for intravenous infusion only. Prepare KANUMA using the following steps.

1. Determine the number of vials needed based on the patient's weight and the recommended dose of 1 mg/kg, 3 mg/kg, or 5 mg/kg using the following calculations (a-b):
  1. Total dose (mg) = Patient's weight (kg) × Recommended dose (mg/kg)
  2. Total number of vials = Total dose (mg) divided by 20 mg/vial
2. Round to the next whole vial and remove the required number of vials from the refrigerator to allow them to reach room temperature.
  1. Volume (mL) of calculated total dose = Total dose (mg) divided by the 2 mg/mL concentration
  2. Volume (mL) of 0.9% Sodium Chloride for dilution = Total infusion volume (mL) for patient's weight (see Table 1) - Volume (mL) of calculated total dose
  Table 1: Total Infusion Volumes [The infusion volume should be based on the prescribed dose and should be prepared to a final KANUMA concentration of 0.1 mg/mL to 1.5 mg/mL.]
  Weight Range (kg) | 1 mg/kg dose | 3 mg/kg dose | 5 mg/kg dose
  Weight Range (kg) | Total Infusion Volume (mL) | Total Infusion Volume (mL) | Total Infusion Volume (mL)
  Weight Range (kg) | 1 to 2.9 | 4 | 8 | 12
  3 to 5.9 | 6 | 12 | 20
  6 to 10.9 | 10 | 25 | 50
  11 to 24.9 | 25 | 50 | 150
  25 to 49.9 | 50 | 100 | 250
  50 to 99.9 | 100 | 250 | 500
  100 to 120.9 | 250 | 500 | 600
3. Mix gently by inversion. Do not shake the vials or the prepared infusion.
4. The solution should be inspected visually for particulate matter and discoloration prior to administration. The solution should be a clear to slightly opalescent, colorless to slightly colored solution. Thin, translucent particles or fibers may be present in the vials or diluted solution. Do not use if the solution is cloudy or if other particulate matter is observed.
5. Vials are for single-use only. Discard any unused product. Do not freeze.

2.4 Administration Instructions

Administer the diluted solution as an intravenous infusion using a low-protein binding infusion set with an in-line, low-protein binding 0.2 micron filter.

Infuse over at least 2 hours. Consider further prolonging the infusion time for patients receiving dosages greater than 1 mg/kg or those who have experienced hypersensitivity reactions [see Warnings and Precautions (5.1)]. A 1-hour infusion may be considered for those patients receiving the 1 mg/kg dose who tolerate the infusion.

2.5 Storage of Diluted Solution

KANUMA contains no preservatives; therefore, product should be used immediately after dilution. If immediate use is not possible, the diluted product may be stored up to 24 hours in the refrigerator at 2°C to 8°C (36°F to 46°F). Do not freeze or shake. Protect from light.

3 DOSAGE FORMS AND STRENGTHS

Injection: 20 mg/10 mL (2 mg/mL) clear to slightly opalescent, colorless to slightly colored solution in single-dose vials.

4 CONTRAINDICATIONS

None.

5 WARNINGS AND PRECAUTIONS

5.1 Hypersensitivity Reactions Including Anaphylaxis

Life-threatening hypersensitivity reactions, including anaphylaxis, have been reported in patients treated with enzyme replacement therapies, including KANUMA. These reactions in KANUMA-treated patients were based on application of Sampson criteria to identify signs/symptoms consistent with anaphylaxis. In clinical trials, 3 (infants) of 106 (3%) patients treated with KANUMA experienced signs and symptoms consistent with anaphylaxis. These patients experienced reactions during infusion with signs and symptoms including chest discomfort, conjunctival injection, dyspnea, generalized and itchy rash, hyperemia, swelling of eyelids, rhinorrhea, severe respiratory distress, tachycardia, tachypnea, and urticaria.

In clinical trials, 21 of 106 (20%) KANUMA-treated patients, including 9 of 14 (64%) infants and 12 of 92 (13%) pediatric patients who were 4 years and older and adults, experienced signs and symptoms either consistent with or that may be related to a hypersensitivity reaction. Signs and symptoms of hypersensitivity reactions, occurring in two or more patients, included abdominal pain, agitation, fever, chills, diarrhea, eczema, edema, hypertension, irritability, laryngeal edema, nausea, pallor, pruritus, rash, and vomiting. The majority of reactions occurred during or within 4 hours of the completion of the infusion. Patients were not routinely pre-medicated prior to infusion of KANUMA in these clinical trials.

Anaphylaxis has occurred during the early course of enzyme replacement therapy and after extended duration of therapy. Administration of KANUMA should be supervised by a healthcare provider knowledgeable in the management of hypersensitivity reactions including anaphylaxis. Initiate KANUMA in a healthcare setting with appropriate medical monitoring and support measures, including access to cardiopulmonary resuscitation equipment. Observe patients closely during and after the infusion.

The management of hypersensitivity reactions should be based on the severity of the reaction and may include temporarily interrupting the infusion, lowering the infusion rate, and/or treatment with antihistamines, antipyretics, and/or corticosteroids. If a severe hypersensitivity reaction (e.g., anaphylaxis) occurs, discontinue KANUMA and immediately initiate appropriate medical treatment, including use of epinephrine. If interrupted, the infusion may be resumed at a slower rate with increases as tolerated. Pre-treatment with antipyretics and/or antihistamines may prevent subsequent reactions in those cases where symptomatic treatment was required.

Inform patients of the symptoms of life-threatening hypersensitivity reactions, including anaphylaxis and to seek immediate medical care should symptoms occur.

Consider the risks and benefits of re-administering KANUMA following a severe reaction. Monitor patients, with appropriate resuscitation measures available, if the decision is made to re-administer the product.

5.2 Hypersensitivity to Eggs or Egg Products

KANUMA is produced in the egg whites of genetically engineered chickens. Patients with a known history of egg allergies were excluded from the clinical trials. Consider the risks and benefits of treatment with KANUMA in patients with known systemic hypersensitivity reactions to eggs or egg products.

6 ADVERSE REACTIONS

6.1 Clinical Trials Experience

Because clinical trials are conducted under widely varying conditions, adverse reaction rates observed in the clinical trials of a drug cannot be directly compared to rates in the clinical trials of another drug and may not reflect the rates observed in clinical practice.

In clinical trials, a total of 106 patients received treatment with KANUMA. The data described below reflect exposure to KANUMA in 75 patients who received KANUMA at dosages up to 3 mg/kg once weekly in clinical trials:

- Nine patients (5 males, 4 females) who had growth failure or other evidence of rapidly progressive LAL deficiency presenting within the first 6 months of life received KANUMA for up to 165 weeks (median 60 weeks) at escalating doses ranging between 0.35 mg/kg and 5 mg/kg once weekly [see Clinical Studies (14.1)].
- 66 pediatric and adult patients with LAL deficiency aged 4 to 58 years (33 males, 33 females) received KANUMA 1 mg/kg every other week for up to 36 weeks.

Table 2 summarizes the most common adverse reactions occurring in >30% of patients with rapidly progressive LAL deficiency presenting within the first 6 months of life receiving KANUMA in Study 1.

Table 2: Adverse Reactions in ≥30% of Infants with Rapidly Progressive LAL Deficiency Presenting within the First 6 Months of Life Receiving KANUMA
Adverse Reactions | KANUMA N=9
Adverse Reactions | n (%)
Diarrhea | 6 (67)
Vomiting | 6 (67)
Fever | 5 (56)
Rhinitis | 5 (56)
Anemia | 4 (44)
Cough | 3 (33)
Nasopharyngitis | 3 (33)
Urticaria | 3 (33)

Other less common adverse reactions reported in patients with rapidly progressive disease presenting within the first 6 months of life who received KANUMA included hypotonia, decreased oxygen saturation, retching, sneezing, and tachycardia.

For infant patients within Study 1 and Study 3 (n = 19), the following additional adverse reactions were reported in ≥ 30% of infants who received KANUMA since the time of marketing authorization, including patients who received an escalated dose to 5 mg/kg qw: hypersensitivity, respiratory distress, and tachycardia.

Table 3 summarizes the most common adverse reactions that occurred in ≥8% of pediatric and adult patients with LAL deficiency receiving KANUMA in Study 2.

Table 3: Adverse Reactions in ≥8% of Pediatric and Adult Patients with LAL Deficiency Receiving KANUMA
Adverse Reactions | KANUMA N = 36 | Placebo N = 30
Adverse Reactions | n (%) | n (%)
Headache | 10 (28) | 6 (20)
Fever | 9 (25) | 7 (23)
Oropharyngeal pain | 6 (17) | 1 (3)
Nasopharyngitis | 4 (11) | 3 (10)
Asthenia | 3 (8) | 1 (3)
Constipation | 3 (8) | 1 (3)
Nausea | 3 (8) | 2 (7)

Other less common adverse reactions reported in pediatric and adult patients who received KANUMA included anxiety and chest discomfort.

For pediatric and adult patients (n = 106), the following additional adverse reactions were reported in ≥ 8% of pediatric and adult patients who received KANUMA since the time of marketing authorization, including patients who received an escalated dose to 3 mg/kg qw: hypersensitivity, diarrhea, abdominal pain, and dizziness.

Hyperlipidemia

Increases in circulating LDL-cholesterol (LDL-c) and triglycerides above pre-treatment values were observed in 29 of 36 (81%) and 21 of 36 (58%) patients, respectively, at 2 and 4 weeks following initiation of KANUMA [see Clinical Pharmacology (12.2)]. The maximum mean percentage increase was 18% for LDL-c at Week 2 and 5% for triglycerides at Week 4.

6.2 Immunogenicity

As with all therapeutic proteins, there is potential for immunogenicity. The detection of antibody formation is highly dependent on the sensitivity and specificity of the assay and may be influenced by several factors including assay methodology, sample handling, timing of sample collection, concomitant medications, and underlying disease. For these reasons, comparison of the incidence of antibodies in the studies described below with the incidence of antibodies in other studies or to other sebelipase alfa products may be misleading.

Approximately 8% (9/106) of pediatric and adult patients with LAL deficiency developed antibodies to sebelipase alfa (anti-drug antibodies or ADA) following treatment with KANUMA across all clinical studies. Among the 9 patients who developed ADA, 2 patients were positive for neutralizing antibodies (NAb). Approximately 53% (10/19) of infants with rapidly progressive LAL deficiency developed ADA following treatment with KANUMA across all clinical studies. Among the 10 patients who developed ADA, 9 patients were positive for NAb.

Study 1: Patients with Rapidly Progressive LAL Deficiency Presenting within the First 6 Months of Life

Seven of the 9 infants with rapidly progressive disease had at least one post-treatment ADA assessment, and 4 of these 7 (57%) patients developed ADA during treatment with KANUMA. All of the 4 ADA-positive patients were determined to be positive for neutralizing antibodies that inhibit in vitro enzyme activity and/or cellular uptake of the enzyme. At the time of initial ADA positivity, 3 patients were receiving a dosage of 1 mg/kg once weekly and 1 patient was receiving a dosage of 3 mg/kg once weekly. Three of the 4 ADA-positive patients had ADA titers monitored from the initiation of treatment and developed measurable ADA titers within the first 2 months of exposure. Persistent ADA was observed in all 4 patients.

Hypersensitivity reactions occurred in all 4 of the ADA-positive patients, whereas they occurred in only 1 of the 3 ADA-negative patients. None of the patients discontinued treatment. In 1 patient, decreased growth velocity in a setting of neutralizing antibodies to KANUMA was observed.

Study 2: Pediatric and Adult Patients with LAL Deficiency

Five of 35 (14%) KANUMA-treated pediatric and adult patients who completed the 20-week double-blind period of study treatment developed ADA. All patients were receiving 1 mg/kg once every other week. All 5 ADA-positive patients first developed measurable ADA titers within the first 3 months of exposure. Two of the 5 ADA-positive patients had a measurable ADA titer at only one time point. In the 3 patients with measurable ADA titers at multiple time points, ADA titers decreased to undetectable levels during continued treatment. Two patients developed in vitro neutralizing antibodies during the open-label extension phase after 20 weeks and 52 weeks of treatment with KANUMA, respectively. There is no clear association between the development of ADA and decreased efficacy in pediatric and adult patients treated with KANUMA.

8 USE IN SPECIFIC POPULATIONS

8.1 Pregnancy

Risk Summary

Available data with KANUMA use in pregnant women are insufficient to identify a drug-associated risk of major birth defects, miscarriage or other adverse maternal or fetal outcomes. Animal reproductive studies conducted with sebelipase alfa showed no evidence of embryolethality, fetotoxicity, teratogenicity, or abnormal early embryonic development at dosages up to 164 and 526 times the human dosage of 1 mg/kg every other week (based on AUC) in rats and rabbits, respectively.

The background risk of major birth defects and miscarriage for the indicated population is unknown. In the U.S. general population, the estimated background risk of major birth defects and miscarriage in clinically recognized pregnancies is 2 to 4% and 15 to 20%, respectively.

Animal Data

Sebelipase alfa administered during the period of organogenesis to rats (on gestation days 6, 9, 12, 15 and 17) and rabbits (on gestation days 7, 10, 13, 16 and 19) at intravenous doses up to 60 and 50 mg/kg, respectively, (approximately 164 and 526 times the human AUC of 1387 ng.h/mL at 1 mg/kg dose administered once every other week, respectively) did not cause any adverse effects on embryofetal development. A pre- and post-natal development study in rats showed no evidence of adverse effects on pre- and postnatal development at intravenous doses (administered on gestation days 6, 9, 12, 15, 18, and 20 and days 4, 7, 10, 14, and 17 postpartum) of sebelipase alfa up to 60 mg/kg/day (approximately 164 times the human AUC of 1387 ng.h/mL at 1 mg/kg dose administered once every other week).

8.2 Lactation

Risk Summary

There are no data on the presence of sebelipase alfa in human milk, the effects on the breastfed infant, or the effects on milk production. It is not known if sebelipase alfa is present in animal milk. The developmental and health benefits of breastfeeding should be considered along with the mother's clinical need for KANUMA and any potential adverse effects on the breastfed infant from sebelipase alfa or from the underlying maternal condition.

8.4 Pediatric Use

Safety and effectiveness of KANUMA have been established in pediatric patients aged 1 month and older. Clinical trials with KANUMA were conducted in 56 pediatric patients (range 1 month to <18 years old) [see Clinical Studies (14)].

8.5 Geriatric Use

Clinical trials of KANUMA did not include any patients aged 65 years old and older. It is not known whether they respond differently than younger patients.

11 DESCRIPTION

Sebelipase alfa is a recombinant human lysosomal acid lipase (rhLAL) that is a lysosomal glycoprotein enzyme produced by recombinant DNA technology in the egg white of eggs laid by genetically engineered chickens. Purified sebelipase alfa is a monomeric glycoprotein containing 6 N-linked glycosylation sites and has a molecular mass of approximately 55 kDa. The amino acid sequence for sebelipase alfa is the same as the amino acid sequence for human LAL. The specific activity of sebelipase alfa is 195 to 345 units/mg. One unit is the amount of enzyme activity that catalyzes the hydrolysis of 1 micromole of the synthetic substrate 4-methylumbelliferyl oleate per minute at 37°C under specified assay conditions.

KANUMA (sebelipase alfa) injection is supplied as a sterile, preservative-free, non-pyrogenic clear to slightly opalescent, colorless to slightly colored aqueous solution in single-dose vials for intravenous infusion. Each vial contains sebelipase alfa 20 mg/10 mL. Each mL of solution contains sebelipase alfa (2 mg), citric acid monohydrate (1.57 mg), Human Serum Albumin (10 mg), and trisodium citrate dihydrate (13.7 mg) at pH 5.9.

12 CLINICAL PHARMACOLOGY

12.1 Mechanism of Action

LAL deficiency is an autosomal recessive lysosomal storage disorder characterized by a genetic defect resulting in a marked decrease or loss in activity of the lysosomal acid lipase (LAL) enzyme. The primary site of action of the LAL enzyme is the lysosome, where the enzyme normally causes the breakdown of lipid particles, including LDL-c and triglycerides. Deficient LAL enzyme activity results in progressive complications due to the lysosomal accumulation of cholesteryl esters and triglycerides in multiple organs, including the liver, spleen, intestine, and the walls of blood vessels. The resulting lipid accumulation in the liver may lead to increased liver fat content and progression of liver disease, including fibrosis and cirrhosis. Lipid accumulation in the intestinal wall leads to malabsorption and growth failure. In parallel, dyslipidemia due to impaired degradation of lysosomal lipid is common with elevated LDL-c and triglycerides and low HDL-cholesterol (HDL-c).

Sebelipase alfa binds to cell surface receptors via glycans expressed on the protein and is subsequently internalized into lysosomes. Sebelipase alfa catalyzes the lysosomal hydrolysis of cholesteryl esters and triglycerides to free cholesterol, glycerol and free fatty acids.

12.2 Pharmacodynamics

In clinical trials, after initiation of dosing with KANUMA, breakdown of accumulated lysosomal lipid led to initial increases in LDL-c and triglycerides within the first 2 to 4 weeks of treatment. In general, following increases in LDL-c and triglycerides, these parameters decreased to below pre-treatment values within 8 weeks of treatment with KANUMA.

In all patients with elevated alanine aminotransferase (ALT) values at baseline (82 of 84 patients in clinical trials), reductions in ALT values were observed, generally within 2 weeks after initiation of treatment with KANUMA. Treatment interruption resulted in increases in LDL-c and ALT values and decreases in HDL-c.

12.3 Pharmacokinetics

The pharmacokinetic profile of sebelipase alfa was nonlinear with a greater than dose-proportional increase in exposure between 1 and 3 mg/kg based on non-compartmental analysis of data from 26 adults. No accumulation was observed following once weekly or once every other week dosing.

Using a population pharmacokinetic model, sebelipase alfa pharmacokinetic parameters were estimated for 65 pediatric and adult patients who received intravenous infusions of KANUMA at 1 mg/kg at Week 22 (Table 4); 24 patients were 4 to 11 years old, 23 were 12 to 17 years old, and 18 were adults. The pharmacokinetic profiles of sebelipase alfa were similar between adolescents and adults. The Tmax and T1/2 were similar across all age groups.

Table 4: Mean (SD) Pharmacokinetics Parameters at Week 22 in Pediatric and Adult Patients Receiving 1 mg/kg Once Every Other Week
Parameter | 4-11 years old | 12-17 years old | ≥18 years old
Parameter | N=24 | N=23 | N=18
AUC (ng∙hr/mL) | 942 (388) | 1454 (699) | 1861 (599)
Cmax (ng/mL) | 490 (205) | 784 (480) | 957 (303)
Tmax (hr) | 1.3 (0.6) | 1.1 (0.3) | 1.3 (0.6)
CL (L/hr) | 31.1 (7.1) | 37.4 (12.4) | 38.2 (12.5)
Vc (L) | 3.6 (3.0) | 5.4 (2.4) | 5.3 (1.6)
T1/2 (min) | 5.4 (4.3) | 6.6 (3.7) | 6.6 (3.7)
Parameter values were estimated using a population pharmacokinetic model.
AUC = Area under the plasma concentration time curve. Cmax = Maximum concentration.
Tmax = Time to maximum concentration. CL = Clearance. Vc = Central volume of distribution. T1/2 = Half-life.

13 NONCLINICAL TOXICOLOGY

13.1 Carcinogenesis, Mutagenesis, Impairment of Fertility

Long-term studies in animals to evaluate carcinogenic potential or studies to evaluate mutagenic potential have not been performed with sebelipase alfa. Sebelipase alfa at intravenous doses up to 60 mg/kg administered twice weekly (approximately 164 times the human AUC of 1387 ng.h/mL at 1 mg/kg dose administered once every other week) was found to have no adverse effect on fertility and reproductive performance of male and female rats.

13.2 Animal Toxicology and/or Pharmacology

In a rat disease model of LAL deficiency that exhibits several abnormalities analogous to the human disease, sebelipase alfa administered intravenously at dosages up to 3 mg/kg once weekly showed improvements in survival, body weight gain, organ weight reduction, reduction in serum transaminases (ALT and aspartate aminotransferase [AST]), reduction in serum and hepatic lipids, and improvement in liver histopathology.

14 CLINICAL STUDIES

14.1 Infants with Rapidly Progressive LAL Deficiency Presenting within the First 6 Months of Life

A multicenter, open-label, single-arm clinical study of KANUMA was conducted in 9 infants with LAL deficiency who had growth failure or other evidence of rapidly progressive disease prior to 6 months of age. The age range at entry was 1 to 6 months. Patients received KANUMA at 0.35 mg/kg once weekly for the first 2 weeks and then 1 mg/kg once weekly. Due to suboptimal clinical response, doses in all 6 surviving patients were escalated to 3 mg/kg once weekly, between 4 and 88 weeks (median 11 weeks) after starting treatment at 1 mg/kg.

The efficacy of KANUMA was assessed by comparing the survival of the 9 KANUMA-treated patients (followed in the open-label, single-arm trial) at 12 months of age to the survival in an untreated, historical cohort of 21 patients with a similar age at disease presentation and clinical characteristics. Of the 9 KANUMA-treated patients, 6 patients survived beyond 12 months of age, compared to 0 of 21 patients who survived in the historical cohort, all of whom had died by 8 months of age. The median age of the 6 surviving KANUMA-treated patients was 18.1 months (range 12 to 42.2 months).

Following initiation of treatment with KANUMA 1 mg/kg once weekly, weight-for-age (WFA) z-scores improved in 3 of 5 surviving patients with growth failure, and all 6 surviving patients demonstrated improvements in WFA z-scores following dose escalation to 3 mg/kg once weekly.

Continuation Treatment

Across Study 1 and another study, Study 3, in infants with rapidly progressive LAL Deficiency, 9 patients received successive dose escalations up to 5 mg/kg once weekly due to suboptimal clinical response [see Recommended Dosage (2.2)]. The median duration of exposure to 5 mg/kg for the 9 patients whose doses were escalated to 5 mg/kg once weekly was 33 months (range 27 to 39 months) for patients in Study 1 and 15 months (range 5 to 24 months) in Study 3.

Of the 9 patients whose KANUMA dose was escalated to 5 mg/kg once weekly, 6 were alive at their last follow up at 3 years, and 2 were alive at their last follow up at 5 years. Of these 9 patients, 6 experienced normalization of ALT and/or AST which had remained abnormal on the lower KANUMA dose.

14.2 Pediatric and Adult Patients with LAL Deficiency

The safety and efficacy of KANUMA were assessed in 66 pediatric and adult patients with LAL deficiency, aged 4 to 58 years (71% were less than 18 years old), in a multicenter, double-blind, placebo-controlled trial. Patients were randomized to receive KANUMA at a dosage of 1 mg/kg (n=36) or placebo (n=30) once every other week for 20 weeks in the double-blind period. Sixty-two of the 66 (94%) patients had LDL-c of 130 mg/dL or greater at study entry. The majority of patients (58%) had LDL-c above 190 mg/dL at study entry, and 24% of patients with LDL-c above 190 mg/dL remained on lipid lowering medications.

At the completion of the 20-week double-blind period of the trial, a statistically significant improvement in percent change from baseline in LDL-c was observed in the KANUMA-treated group as compared to the placebo group (mean difference and 95% C.I.: -22%, [-33%, -15%]; p<0.0001). LDL-c of less than 130 mg/dL was achieved in 13 of 32 (41%; 95% C.I.: [24%, 58%]) KANUMA-treated patients and in only 2 of 30 (7%; 95% C.I.: [0%, 16%]) placebo-treated patients with baseline LDL-c of 130 mg/dL or greater. A statistically significant improvement in percent change from baseline at 20 weeks was also observed in the KANUMA-treated group compared to the placebo group for other parameters related to LAL deficiency, including decreases in non-HDL-c (mean difference and 95% C.I.: -21%, [-30%, -15%]; p<0.0001) and triglycerides (mean difference and 95% C.I.: -14%, [-28%, -1%]; p=0.0375), and increases in HDL-c (mean difference and 95% C.I.: 20%, [12%, 26%]; p<0.0001). The effect of KANUMA on cardiovascular morbidity and mortality has not been established.

Patients treated with KANUMA had larger reductions from baseline in ALT values and liver fat content (measured by MRI), compared to patients treated with placebo. The significance of these findings as they relate to progression of liver disease in LAL deficiency has not been established.

Open Label Treatment

Pediatric and adult patients who participated in the randomized, placebo-controlled trial were eligible to continue treatment in an open-label extension. Sixty-five of the 66 patients entered the open-label extension and were treated with KANUMA at a dosage of 1 mg/kg once every other week. During the open-label extension, patients treated with KANUMA for up to 36 weeks demonstrated improvements in lipid parameters, including LDL-c and HDL-c levels, and ALT.

Continuation Treatment

Across Study 2 and another study, Study 4, in children and adults with LAL Deficiency, 23 of 97 patients received dose escalations from the protocol-defined starting dose of 1 mg/kg every other week (12 patients in Study 2 and 11 patients in Study 4). The median duration of exposure to the 3 mg/kg every other week regimen was 28 months (range 6 to 33 months) for patients in Study 2 and 12 months (range 3 to 27 months) in Study 4. Before being escalated to 3 mg/kg every other week, patients were on 1 mg/kg every other week for a median of 19 months (range 6 to 33 months), and most dose escalations were initiated in response to an increase in serum transaminase levels, an increase in serum lipids, or a decrease in WFA z-scores in children.

Of the 23 patients whose KANUMA dose was escalated to 3 mg/kg every other week, 20 were children. After the dose escalation, 14 of the 23 patients experienced normalization of one or more of the following biomarkers which had remained abnormally high on the lower KANUMA dose: serum transaminases, triglycerides, and/or LDL-c.

16 HOW SUPPLIED/STORAGE AND HANDLING

KANUMA (sebelipase alfa) injection is a preservative-free, clear to slightly opalescent, colorless to slightly colored, nonpyrogenic solution supplied as 20 mg/10 mL (2 mg/mL) in single-dose, glass vials.

NDC 25682-007-01: 20 mg/10 mL vial

STORAGE AND HANDLING

Store KANUMA refrigerated at 2°C to 8°C (36°F to 46°F) in original carton to protect from light. Do not shake or freeze the vials.

17 PATIENT COUNSELING INFORMATION

Hypersensitivity Reactions Including Anaphylaxis

Advise patients and caregivers that life-threatening hypersensitivity reactions, including anaphylaxis may occur with KANUMA treatment.

Advise patients and caregivers that anaphylaxis has occurred during the early course of enzyme replacement therapy and after extended duration of therapy.

Inform patients and caregivers of the symptoms of life-threatening hypersensitivity reactions, including anaphylaxis and to seek immediate medical care should symptoms occur [see Warnings and Precautions (5.1)].

Hypersensitivity to Eggs or Egg Products

KANUMA is produced in the egg whites of genetically engineered chickens. Patients with a known history of egg allergies were excluded from the clinical trials. Consider the risks and benefits of treatment with KANUMA in patients with known systemic hypersensitivity reactions to eggs or egg products [see Warnings and Precautions (5.2)].

Manufactured by:
Alexion Pharmaceuticals, Inc.
121 Seaport Boulevard
Boston, MA 02210 USA

US License Number: 1743

KANUMA is a registered trademark of Alexion Pharmaceuticals, Inc.
© 2024 Alexion Pharmaceuticals, Inc.

PRINCIPAL DISPLAY PANEL - 20 mg/10 mL Vial Carton

NDC 25682-007-01
Rx only

Kanuma®
(sebelipase alfa)
Injection

20 mg/10 mL
(2 mg/mL)

For Intravenous Infusion Only
Dilute Before Use
Single-Use Only
Discard Unused Portion

1 vial

ALEXION®